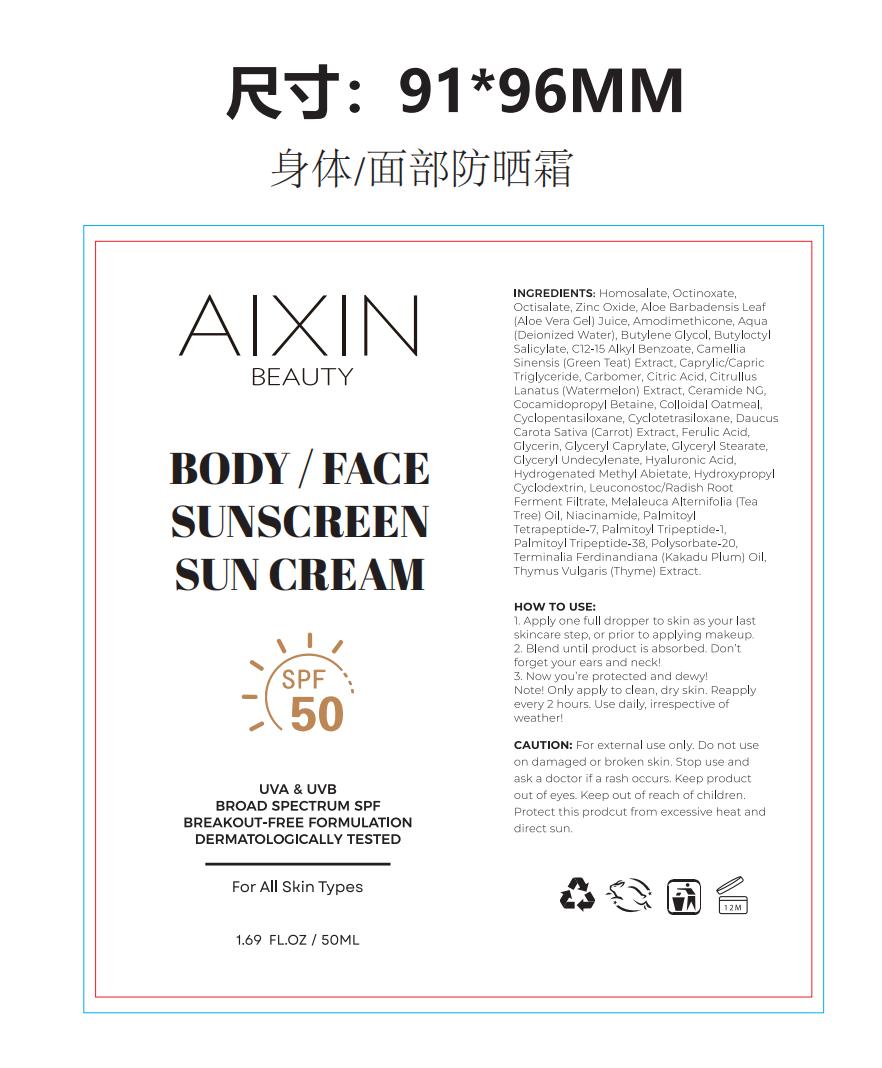 DRUG LABEL: BODY / FACE SUNSCREEN SUN
NDC: 85897-374 | Form: CREAM, AUGMENTED
Manufacturer: Guanghzou AiXin Biotech Co., Ltd
Category: homeopathic | Type: HUMAN OTC DRUG LABEL
Date: 20250703

ACTIVE INGREDIENTS: HOMOSALATE 7.5 g/1 1; OCTINOXATE 7.5 g/1 1
INACTIVE INGREDIENTS: BUTYLENE GLYCOL DICAPRYLATE/DICAPRATE; C12-15 ALKYL BENZOATE; CAPRYLIC/CAPRIC TRIGLYCERIDE; CITRIC ACID; COCAMIDOPROPYL BETAINE; FERULIC ACID; GLYCERYL CAPRYLATE; GLYCERYL STEARATE; HYALURONIC ACID; LEUCONOSTOC/RADISH ROOT FERMENT FILTRATE; MELALEUCA ALTERNIFOLIA (TEA TREE) LEAF; PALMITOYL TETRAPEPTIDE-7; ZINC OXIDE; THYMUS VULGARIS (THYME) OIL; ALOE BARBADENSIS LEAF JUICE; CARBOMER; GLYCERIN; PALMITOYL TRIPEPTIDE-38; AQUA; PENTAMETHYL CYCLOPENTASILOXANE; DAUCUS CAROTA SATIVA (CARROT) SEED OIL; HYDROGENATED METHYL ABIETATE; CITRULLUS LANATUS (WATERMELON) SEED OIL; CERAMIDE NG; BUTYLOCTYL SALICYLATE; CAMELLIA SINENSIS LEAF; NIACINAMIDE; OCTISALATE; AMODIMETHICONE (1300 CST); PALMITOYL TRIPEPTIDE-1

DOSAGE AND ADMINISTRATION

1.69 FL.OZ/50 ML

INACTIVE INGREDIENT

Octisalate,Zinc Oxide,Aloe Barbadensis Leaf (Aloe Vera Gel) Juice,Amodimethicone,Aqua (Deionized Water),Butylene Glycol
Butyloctyl Salicylate,C12-15 Alkyl Benzoate,Camellia Sinensis (Green Teat) Extract,Caprylic/Capric Triglyceride
Carbomer,Citric Acid,Citrullus Lanatus (Watermelon) Extract,Ceramide NG,Cocamidopropyl Betaine,Colloidal Oatmeal
Cyclopentasiloxane,Daucus Carota Sativa (Carrot) Extract,Ferulic Acid, Glycerin,Glyceryl Caprylate,Glyceryl Stearate,
Glyceryl Undecylenate,Hyaluronic Acid,Hydrogenated Methyl Abietate,Hydroxypropyl Cyclodextrin
Leuconostoc/Radish Root Ferment Filtrate,Melaleuca Alternifolia (Tea Tree) Oil,Niacinamide
Palmitoyl Tetrapeptide-7,Palmitoyl Tripeptide-1

ACTIVE INGREDIENT

Homosalate,Octinoxate

KEEP OUT OF REACH OF CHILDREN SECTION

PURPOSE

Sunscreen

WARNINGS

Please put it in a place where children are not in contact

INDICATIONS AND USAGE

Sunscreen